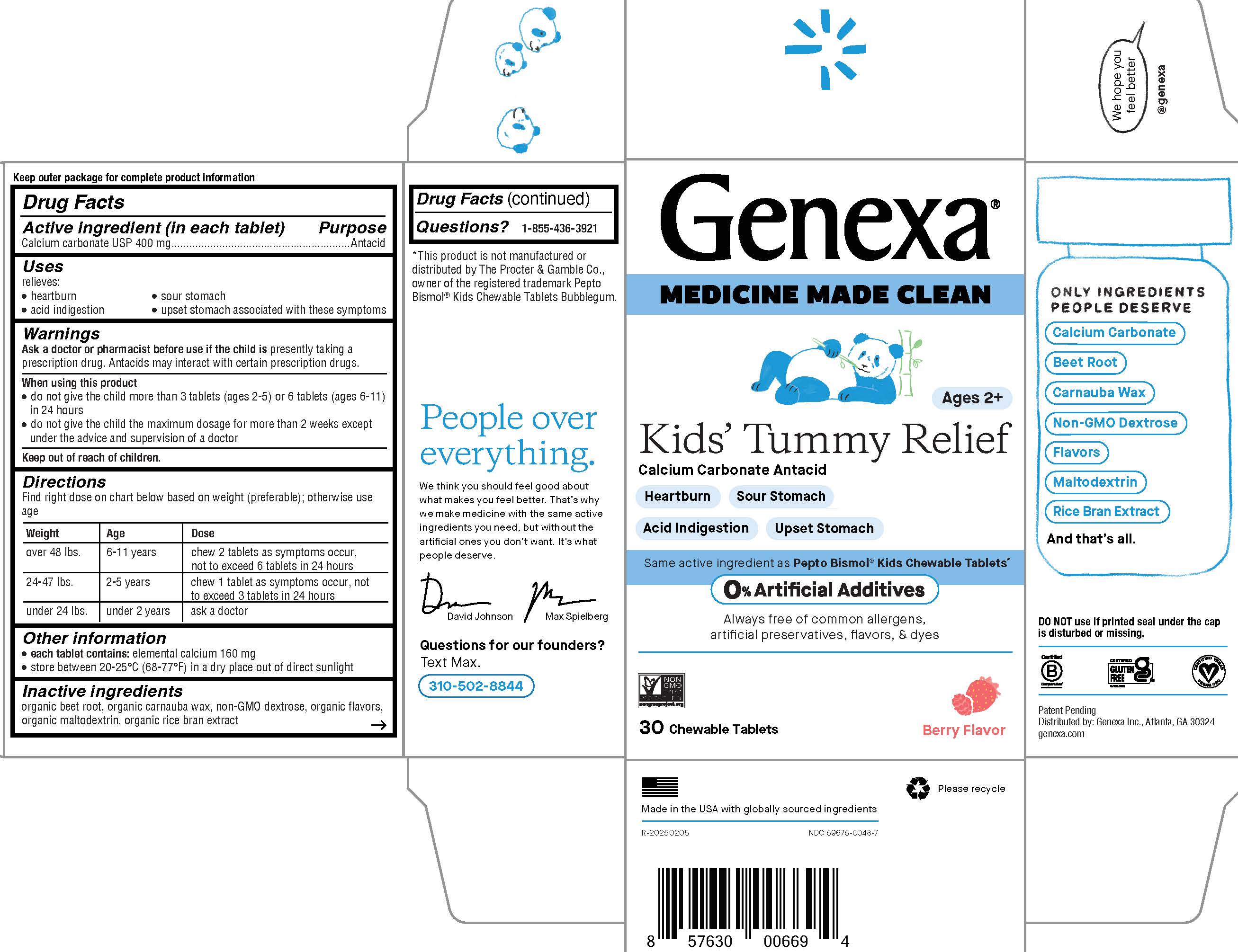 DRUG LABEL: Kids Tummy Relief
NDC: 69676-0043 | Form: TABLET, CHEWABLE
Manufacturer: Genexa Inc.
Category: otc | Type: HUMAN OTC DRUG LABEL
Date: 20250523

ACTIVE INGREDIENTS: CALCIUM CARBONATE 400 mg/1 1
INACTIVE INGREDIENTS: BEET; CARNAUBA WAX; DEXTROSE; MALTODEXTRIN; RICE BRAN

Kids' Tummy Relief

Drug Facts

Active ingredient (in each tablet)

Calcium carbonate USP 400 mg

Purpose

Antacid

Uses

relieves:

- heartburn
- acid indigestion
- sour stomach
- upset stomach associated with these symptoms

Warnings

Ask a doctor or pharmacist before use if the child is presently taking a prescription drug. Antacids may interact with certain prescription drugs.

When using this product

- do not give the child more than 3 tablets (ages 2-5) or 6 tablets (ages 6-11) in 24 hours
- do not give the child the maximum dosage for more than 2 weeks except under the advice and supervision of a doctor

Keep out of reach of children.

Directions

Find right dose on chart below based on weight (preferable); otherwise use age

Weight | Age | Dose
over 48 lbs. | 6-11 years | chew 2 tablets as symptoms occur, not to exceed 6 tablets in 24 hours
24-47 lbs. | 2-5 years | chew 1 tablet as symptoms occur, not to exceed 3 tablets in 24 hours
under 24 lbs. | under 2 years | ask a doctor

Other information

- each tablet contains: elemental calcium 160 mg
- store between 20-25°C (68-77°F) in a dry place out of direct sunlight

Inactive ingredients

organic beet root, organic carnauba wax, non-GMO dextose, organic flavors, organic maltodextrin, organic rice bran extract

Questions?

1-855-436-3921

*This product is not manufactured or distributed by The Procter & Gamble Co., owener of the registered trademark Pepto Bismol® Kids Chewable Tablets Bubblegum.

DO NOT use if printed seal under the cap is disturbed or missing.

Patent Pending

Distributed by: Genexa Inc. Atlanta, GA 30324

genexa.com

Made in the USA with globally sourced ingredients

NDC 69676-0043-7

Uses

relieves:

- heartburn
- acid indigestion
- sour stomach
- upset stomach associated with these symptoms

PACKAGE LABEL

Genexa®

MEDICINE MADE CLEAN

Ages 2+

Kids' Tummy Relief

Calcium Carbonate Antacid

Heartburn

Sour Stomach

Acid Indigestion

Upset Stomach

Same active ingredient as Pepto Bismol® Kids Chewable Tablets*

0% Artificial Additives

Always free of common allergens, artificial preservatives, flavors, & dyes

30 Chewable Tablets

Berry Flavor